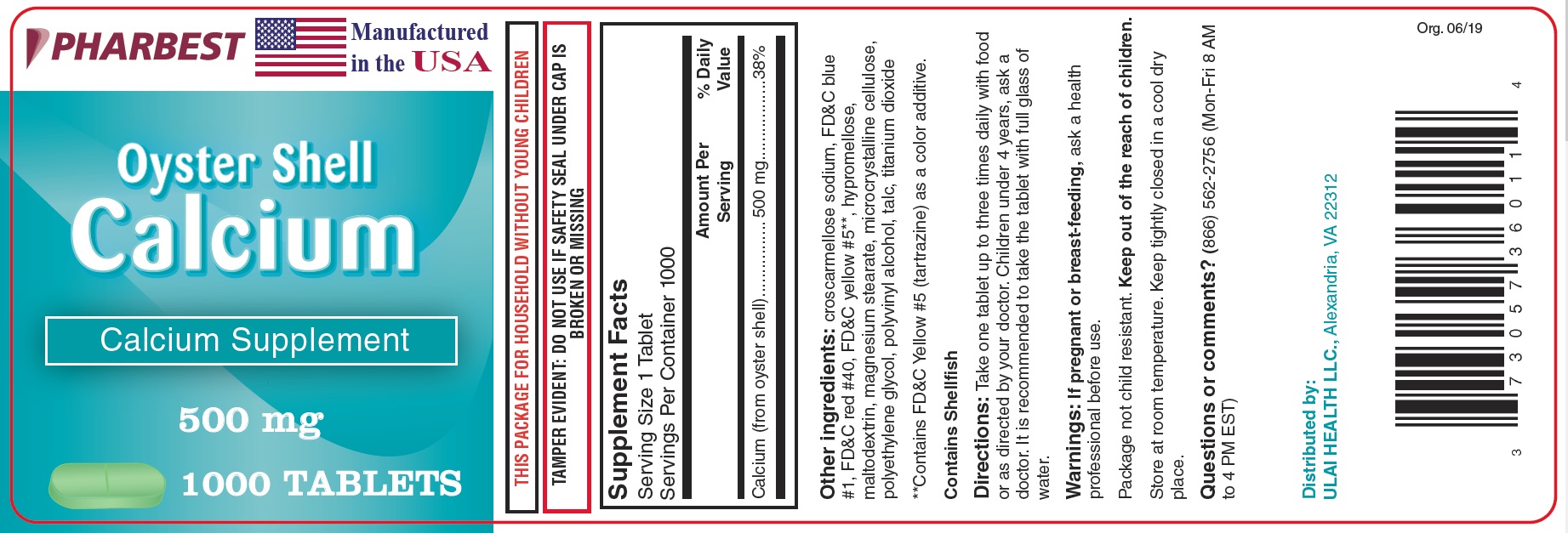 DRUG LABEL: Oyster Shell Calcium
NDC: 73057-360 | Form: TABLET, COATED
Manufacturer: Ulai Health LLC
Category: other | Type: DIETARY SUPPLEMENT
Date: 20190723

ACTIVE INGREDIENTS: CALCIUM CARBONATE 500 mg/1 1
INACTIVE INGREDIENTS: CROSCARMELLOSE SODIUM; FD&C BLUE NO. 1; FD&C RED NO. 40; FD&C YELLOW NO. 5; HYPROMELLOSE, UNSPECIFIED; MALTODEXTRIN; MAGNESIUM STEARATE; CELLULOSE, MICROCRYSTALLINE; POLYETHYLENE GLYCOL, UNSPECIFIED; POLYVINYL ALCOHOL, UNSPECIFIED; TALC; TITANIUM DIOXIDE

Supplement Facts

Serving Size 1 Tablet

Servings Per Container 1000

 | Amount Per Serving | % Daily Value
Calcium (from oyster shell) | 500 mg | 38%

Other ingredients: croscarmellose sodium, FD&C blue #1, FD&C red #40, FD&C yellow #5**, hypromellose, maltodextrin, magnesium stearate, microcrystalline cellulose, polyethylene glycol, polyvinyl alcohol, talc, titanium dioxide

**Contains FD&C Yellow #5 (tartrazine) as a color additive.

Contains Shellfish

Directions:

Take one tablet up to three times daily with food or as directed by your doctor. Children under 4 years, ask a doctor.

it is recommended to take the tablet with full glass of water.

Warnings:

If pregnant or breast-feeding, ask a health professional before use.

Package not child resistant.

Keep out of the reach of children.

SAFE HANDLING WARNING

Store at room temperature. Keep tightly closed in a cool dry place.

Questions or comments? (866) 562-2756 (Mon-Fri 8 AM to 4 PM EST)

PACKAGE LABEL

PHARBEST

Manufactured in the USA

Oyster Shell

Calcium

Calcium Supplement

500 mg

1000 TABLETS